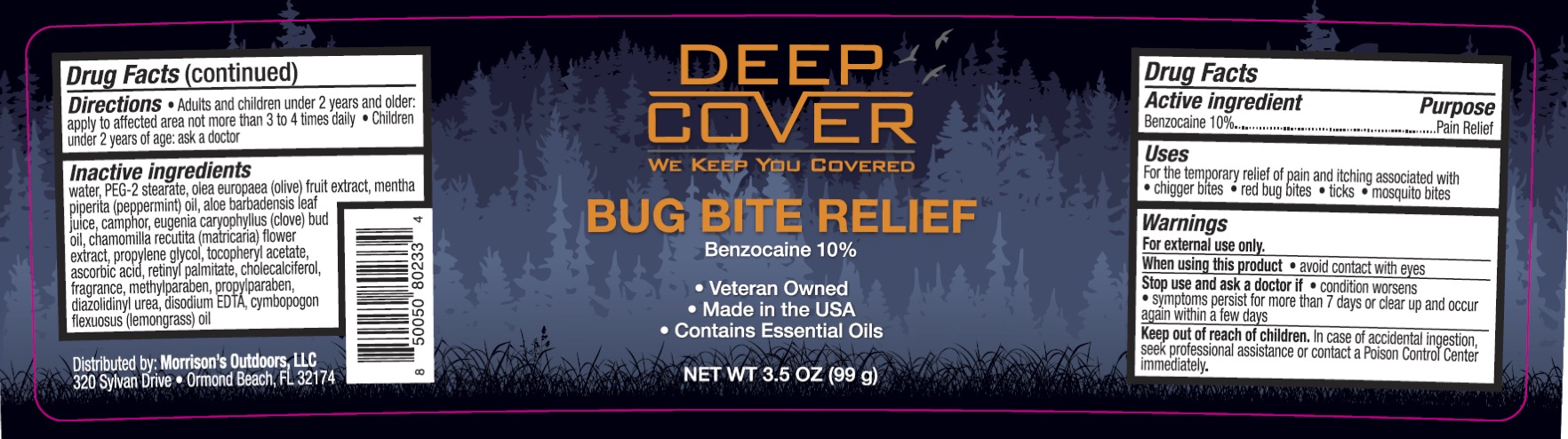 DRUG LABEL: Deep Cover Bug Bite Relief
NDC: 84806-147 | Form: OINTMENT
Manufacturer: Morrisons Outdoors, LLC
Category: otc | Type: HUMAN OTC DRUG LABEL
Date: 20241021

ACTIVE INGREDIENTS: BENZOCAINE 10 g/100 g
INACTIVE INGREDIENTS: LEMONGRASS OIL; CAMPHOR (SYNTHETIC); PEG-2 STEARATE; CLOVE OIL; MATRICARIA CHAMOMILLA FLOWERING TOP OIL; PROPYLENE GLYCOL; PEPPERMINT OIL; .ALPHA.-TOCOPHEROL ACETATE; VITAMIN A PALMITATE; ALOE VERA LEAF; DIAZOLIDINYL UREA; PROPYLPARABEN; EDETATE DISODIUM; ASCORBIC ACID; OLIVE OIL; METHYLPARABEN; WATER; CHOLECALCIFEROL

Deep Cover Bug Bite Relief

ACTIVE INGREDIENT

Benzocaine 10%

PURPOSE

Pain Relief

DOSAGE AND ADMINISTRATION

Uses: for the temporary relief of pain and itching associated with chigger bites, red bug bites, ticks, and mosquito bites.

WARNINGS

For external use only.

When using this product avoid contact with eyes. Stop use and ask a doctor if the condition worsens, symptoms persist for more than 7 days or clear up and occur again within a few days.

KEEP OUT OF REACH OF CHILDREN

In case of accidental ingestion, seek professional assistance or contact a Poison Control Center immediately.

INDICATIONS AND USAGE

Adults and children 2 years and older: apply to the affected area, not more than 3 to 4 times daily. Children under 2 years of age: ask a doctor.

INACTIVE INGREDIENT

Water, PEG-2 Stearate, Olea Europaea (Olive) Fruit Extract, Mentha Piperita (Peppermint) Oil, Aloe Barbadensis Leaf Extract, Camphor, Eugenia Caryophyllus (Clove) Flower Oil, Chamomilla Recutita (Matricaria) Flower Extract, Propylene Glycol, Tocopheryl Acetate, Ascorbic Acid, Retinyl Palmitate, Cholecalciferol, Fragrance, Methylparaben, Propylparaben, Diazolidinyl Urea, Disodium EDTA, Cymbopogon Flexuosus (Lemongrass) Oil,